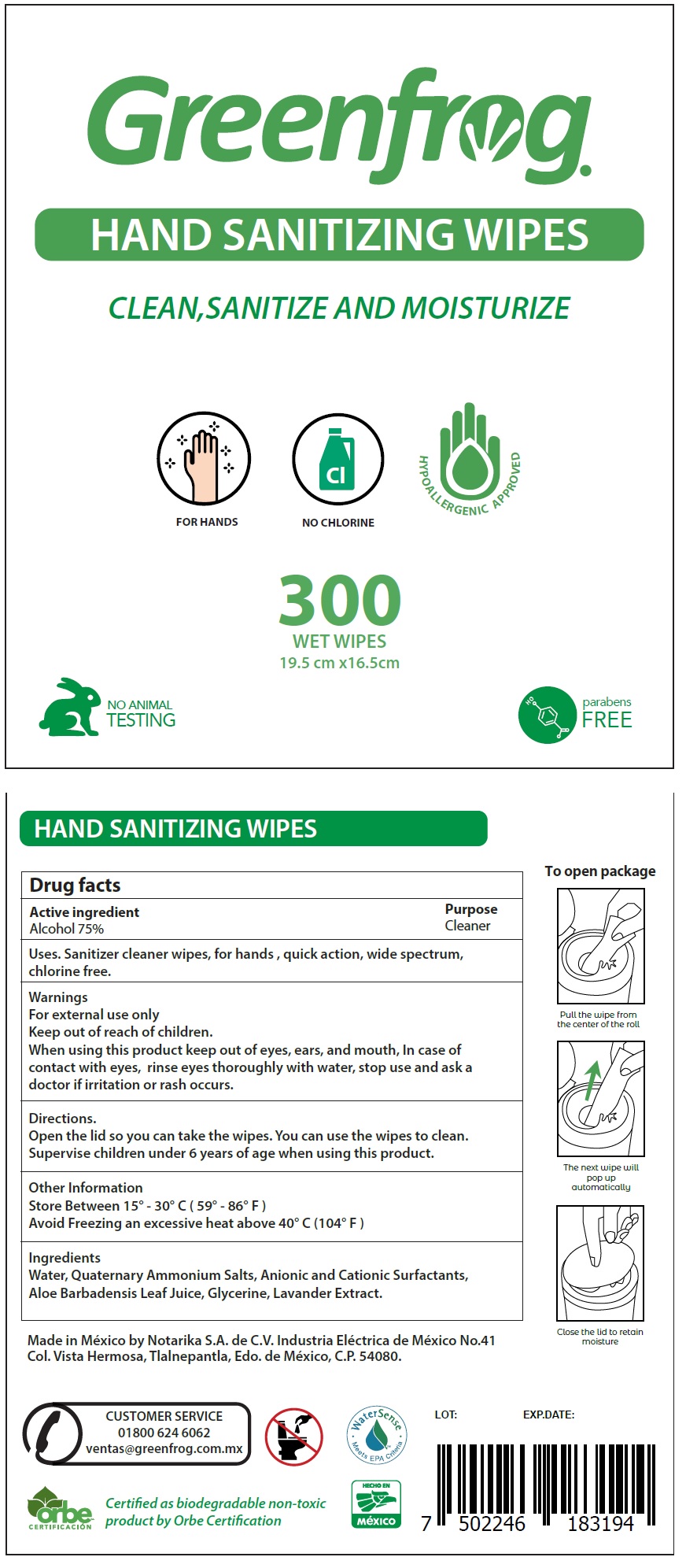 DRUG LABEL: Greenfrog Hand Sanitizing Wipes
NDC: 77145-002 | Form: CLOTH
Manufacturer: Notarika, S.A. de C.V.
Category: otc | Type: HUMAN OTC DRUG LABEL
Date: 20220103

ACTIVE INGREDIENTS: ALCOHOL 75 mL/100 mL
INACTIVE INGREDIENTS: WATER; ALOE VERA LEAF; GLYCERIN; LAVANDULA ANGUSTIFOLIA SUBSP. ANGUSTIFOLIA FLOWER

Greenfrog Hand Sanitizing Wipes

Active ingredient

Alcohol 75%

Purpose

Cleaner

Uses.

Sanitizer cleaner wipes, for hands , quick action, wide spectrum, chlorine free.

Warnings

For external use only

When using this product

keep out of eyes, ears, and mouth, In case of contact with eyes, rinse eyes thoroughly with water,

stop use and ask a doctor

if irritation or rash occurs.

Directions.

Open the lid so you can take the wipes. You can use the wipes to clean.
Supervise children under 6 years of age when using this product.

Other Information

Store Between 15° - 30° C (59° - 86° F)
Avoid Freezing an excessive heat above 40° C (104° F)

Ingredients

Water, Quaternary Ammonium Salts, Anionic and Cationic Surfactants, Aloe Barbadensis Leaf Juice, Glycerine, Lavander Extract.